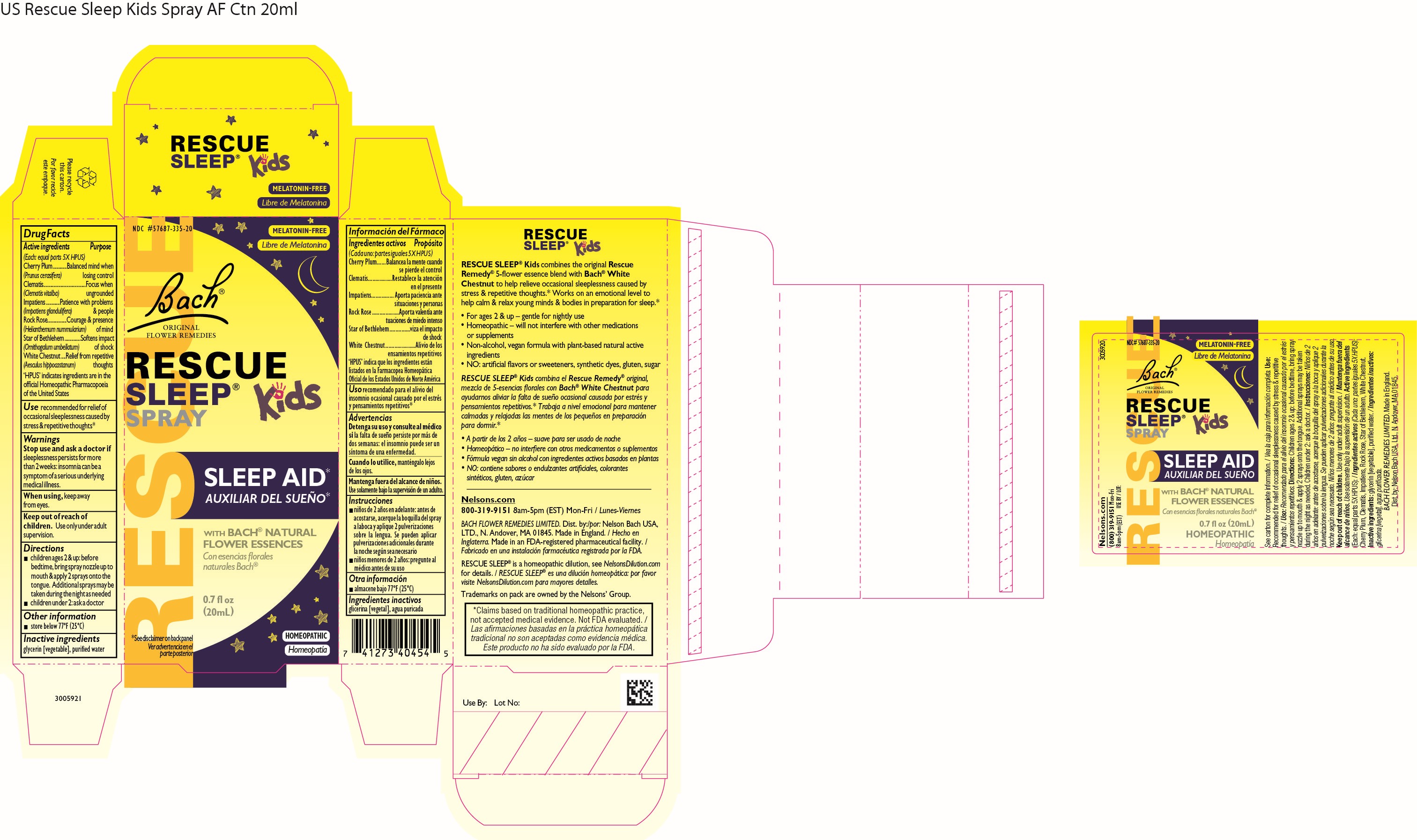 DRUG LABEL: Rescue Sleep Kids
NDC: 57687-335 | Form: SPRAY
Manufacturer: Nelson Bach USA Limited
Category: homeopathic | Type: HUMAN OTC DRUG LABEL
Date: 20240625

ACTIVE INGREDIENTS: ORNITHOGALUM UMBELLATUM FLOWERING TOP 5 [hp_X]/0.095 mL; PRUNUS CERASIFERA FLOWER 5 [hp_X]/0.095 mL; CLEMATIS VITALBA FLOWER 5 [hp_X]/0.095 mL; HELIANTHEMUM NUMMULARIUM FLOWER 5 [hp_X]/0.095 mL; AESCULUS HIPPOCASTANUM FLOWER 5 [hp_X]/0.095 mL; IMPATIENS GLANDULIFERA FLOWER 5 [hp_X]/0.095 mL
INACTIVE INGREDIENTS: GLYCERIN; WATER

Rescue Remedy Sleep Kids Spray

Drug Facts - Active Ingredients

Drug Facts

Active Ingredients (Each: equal parts 5X HPUS)

Purpose

Cherry Plum (Prunus cerasifera) - Balanced mind when losing control

Clematis (Clematis vitalba) - Focus when undgrounded

Impatiens (Impatiens glandulifera) - Patience with problems & people

Rock Rose (Helianthemum nummularium) - Courage & presence of mind

Star of Bethlehem (Ornithogalum umbellatum) - Softens impact of shock

White Chestnut (Aesculus hippocastanum) - Relief from repetitive thoughts

'HPUS' indicates ingredients are in the official Homeopathic Pharmacopoeia of the United States

Use

recommended for relief of occasional sleeplessness caused by stress & repetitive thoughts 1

1 Claims based on traditional homeopathic practice, not accepted medical evidence. Not FDA evaluated.

Warnings

Stop use and ask a doctor if sleeplessness persists for more than 2 weeks: insomnia can be a symptom of a serious underlying
medical illness.
When using, keep away from eyes.
Keep out of reach of children.

Use only under adult supervision.

Directions

children ages 2 & up: before bedtime, bring spray nozzle up to mouth & apply 2 sprays onto the tongue. Additional sprays may be
taken during the night as needed

children under 2: ask a doctor

Other Information

store below 77ºF (25ºC)

Inactive Ingredients

glycerin [vegetable], purified water

Questions

(800) 319-9151 Mon-Fri 8am-5pm (EST)

Distributed by

Dist by

Nelson Bach USA, LTD, N. Andover, MA 01845

OTC Purpose

For the relief of occasional sleplessness

Keep out of reach of children

Primary display panel - Rescue Spray Kids

Rescue Sleep Kids

NDC 57687-335-20

MELATONIN-FREE

Bach ®

ORIGINAL
FLOWER REMEDIES

RESCUE SLEEP®
SPRAY KIDS

SLEEP AID

WITH Bach ®
NATURAL
FLOWER ESSENCES

0.7 fl oz (20mL)
Homeopathic

*See disclaimer
on back panel